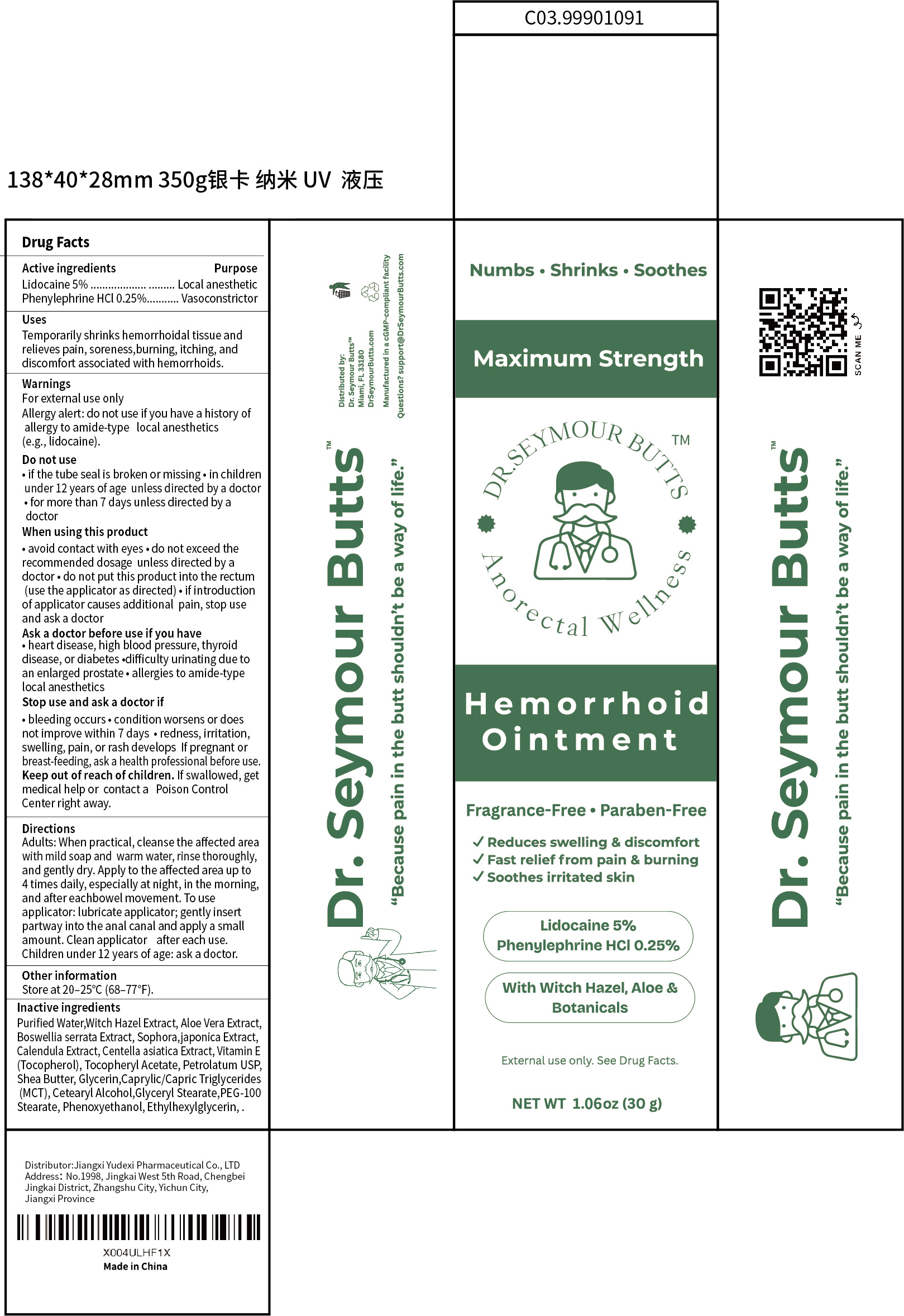 DRUG LABEL: Dr.Seymour Butts  Hemorrhoid
NDC: 85248-018 | Form: OINTMENT
Manufacturer: Jiangxi Yudexi Pharmaceutical Co., LTD
Category: otc | Type: HUMAN OTC DRUG LABEL
Date: 20260129

ACTIVE INGREDIENTS: LIDOCAINE 5 g/100 g; PHENYLEPHRINE HYDROCHLORIDE 0.25 g/100 g
INACTIVE INGREDIENTS: PEG-100 STEARATE; SHEA BUTTER; GLYCERYL STEARATE; CAPRYLIC/CAPRIC TRIGLYCERIDE; WATER; BOSWELLIA SERRATA GUM; PETROLATUM; BAPTISIA ALBA WHOLE; PHENOXYETHANOL; CALENDULA ARVENSIS LEAF; CETOSTEARYL ALCOHOL; ALOE VERA LEAF; SWERTIA JAPONICA WHOLE FLOWERING; .ALPHA.-TOCOPHEROL; ETHYLHEXYLGLYCERIN; CENTELLA ASIATICA TRITERPENOIDS; .ALPHA.-TOCOPHEROL ACETATE; WITCH HAZEL

85248-018

Active Ingredient

Lidocaine 5% Phenylephrine HCl 0.25%

Purpose

Local anesthetic，Vasoconstrictor

Use

Temporarily shrinks hemorrhoidal tissue and relieves pain, soreness,
burning, itching, and discomfort associated with hemorrhoids.

Warnings

For external use only Allergy alert: do not use if you have a history of allergy to amide-type
local anesthetics (e.g., lidocaine).

Do not use

• if the tube seal is broken or missing • in children under 12 years of age
unless directed by a doctor • for more than 7 days unless directed by a
doctor

When Using

• avoid contact with eyes • do not exceed the recommended dosage
unless directed by a doctor • do not put this product into the rectum (use
the applicator as directed) • if introduction of applicator causes additional
pain, stop use and ask a docto

Stop Use

• bleeding occurs • condition worsens or does not improve within 7 days
• redness, irritation, swelling, pain, or rash develops
If pregnant or breast-feeding, ask a health professional before use.

Ask Doctor

• heart disease, high blood pressure, thyroid disease, or diabetes •
difficulty urinating due to an enlarged prostate • allergies to amide-type
local anesthetics

Keep Oot Of Reach Of Children

If swallowed, get medical help or contact a Poison Control Center right away.

Directions

Adults: When practical, cleanse the affected area with mild soap and
warm water, rinse thoroughly, and gently dry. Apply to the affected area
up to 4 times daily, especially at night, in the morning, and after each
bowel movement. To use applicator: lubricate applicator; gently insert
partway into the anal canal and apply a small amount. Clean applicator
after each use.
Children under 12 years of age: ask a doctor.

Other information

Store at 20–25°C (68–77°F).

Inactive ingredients

Purified Water，Witch Hazel Extract, Aloe Vera Extract, Boswellia serrata Extract, Sophora，
japonica Extract, Calendula Extract, Centella asiatica Extract, Vitamin E
(Tocopherol), Tocopheryl Acetate, Petrolatum USP, Shea Butter, Glycerin,
Caprylic/Capric Triglycerides (MCT), Cetearyl Alcohol, Glyceryl Stearate,
PEG-100 Stearate, Phenoxyethanol, Ethylhexylglycerin.